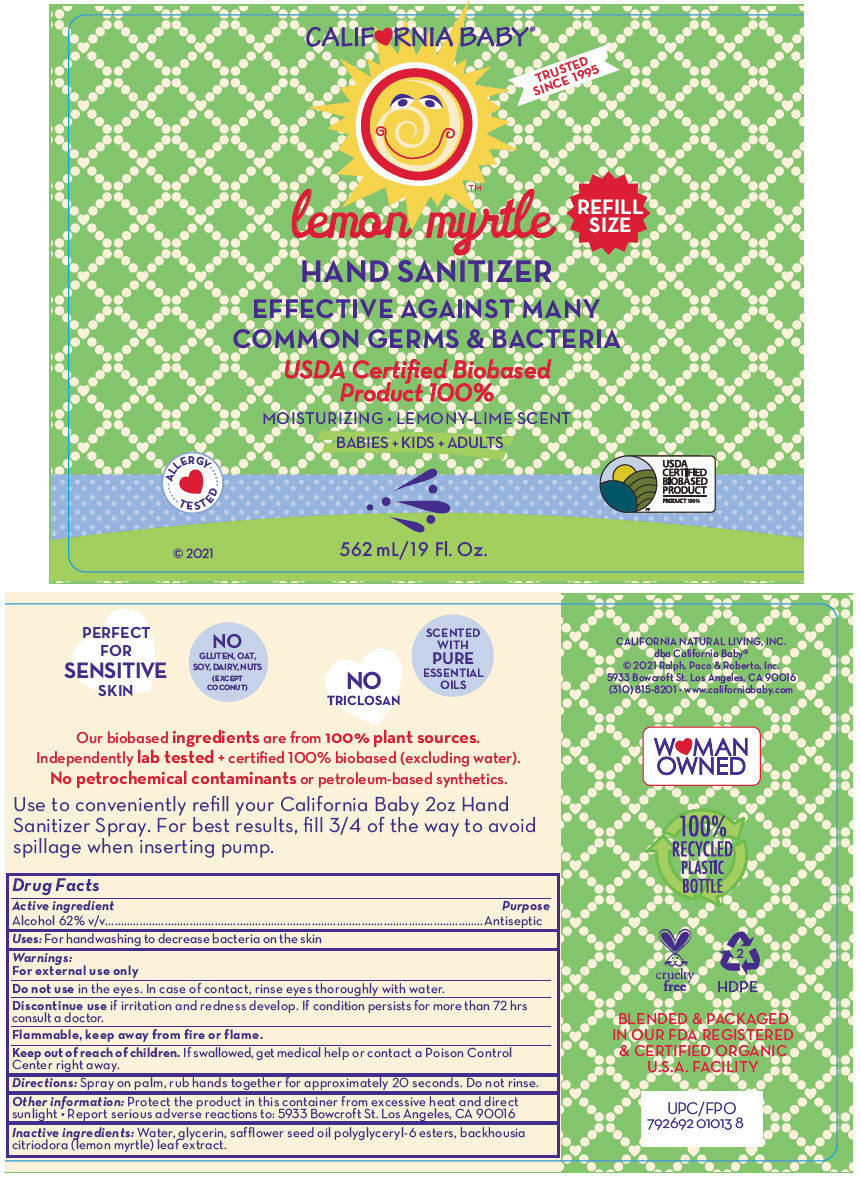 DRUG LABEL: LEMON MYRTLE HAND SANITIZER
NDC: 52915-066 | Form: SPRAY
Manufacturer: ORGANIC & SUSTAINABLE BEAUTY
Category: otc | Type: HUMAN OTC DRUG LABEL
Date: 20241106

ACTIVE INGREDIENTS: ALCOHOL 62 mL/100 mL
INACTIVE INGREDIENTS: WATER; GLYCERIN; SAFFLOWER SEED OIL POLYGLYCERYL-6 ESTERS; BACKHOUSIA CITRIODORA LEAF OIL

LEMON MYRTLE HAND SANITIZER

Drug Facts

Active ingredient

Alcohol 62% v/v

Purpose

Antiseptic

Uses

For handwashing to decrease bacteria on the skin

Warnings

For external use only

Do not use in the eyes. In case of contact, rinse eyes thoroughly with water.

STOP USE

Discontinue use if irritation and redness develop. If condition persists for more than 72 hrs consult a doctor.

Flammable, keep away from fire or flame.

Keep out of reach of children. If swallowed, get medical help or contact a Poison Control Center right away.

Directions

Spray on palm, rub hands together for approximately 20 seconds. Do not rinse.

Other information

Protect the product in this container from excessive heat and direct sunlight

- Report serious adverse reactions to: 5933 Bowcroft St. Los Angeles, CA 90016

Inactive ingredients

Water, glycerin, safflower seed oil polyglyceryl-6 esters, backhousia citriodora (lemon myrtle) leaf extract.

PRINCIPAL DISPLAY PANEL - 562 mL Bottle Label

CALIF♥RNIA BABY®

TRUSTED
SINCE 1995

lemon myrtle

REFILL
SIZE

HAND SANITIZER
EFFECTIVE AGAINST MANY
COMMON GERMS & BACTERIA

USDA Certified Biobased
Product 100%

MOISTURIZING • LEMONY-LIME SCENT

BABIES + KIDS + ADULTS

ALLERGY
TESTED

© 2021

562 mL/19 Fl. Oz.

USDA
CERTIFIED
BIOBASED
PRODUCT
PRODUCT 100%